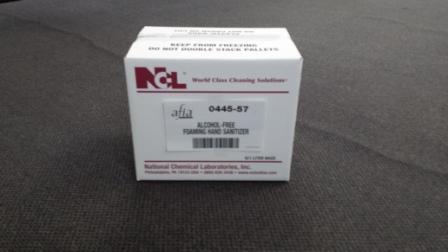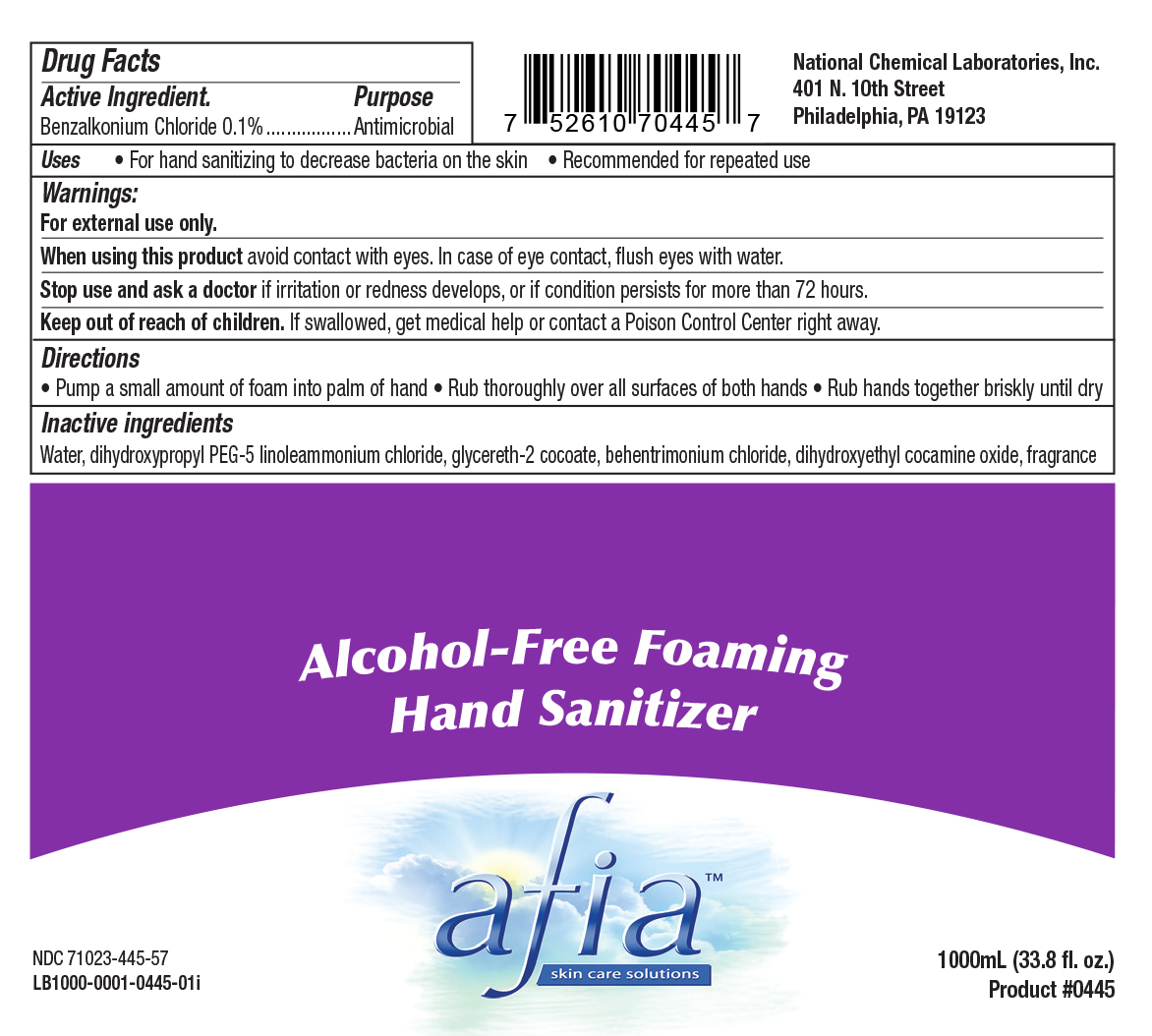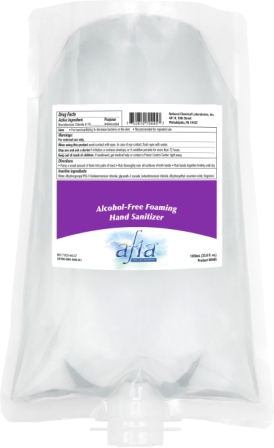 DRUG LABEL: Afia Alcohol-Free Foaming Hand Sanitizer
NDC: 71023-445 | Form: SOAP
Manufacturer: National Chemical Laboratories, Inc.
Category: otc | Type: HUMAN OTC DRUG LABEL
Date: 20221028

ACTIVE INGREDIENTS: BENZALKONIUM CHLORIDE 1 mg/1 mL
INACTIVE INGREDIENTS: GLYCERETH-2 COCOATE; BEHENTRIMONIUM CHLORIDE; DIHYDROXYETHYL COCAMINE OXIDE; DIHYDROXYPROPYL PEG-5 LINOLEAMMONIUM CHLORIDE; WATER

Listing of Alcohol-Free Foaming Hand Sanitizer in multiple packages

Drug Facts

Active Ingredient. Purpose

Benzalkonium Chloride 0.1%...........Antimicrobial

Uses

- For hand sanitizing to decrease bacteria on the skin
- Recommended for repeated use

Warnings:

For external use only.

When using this product avoid contact with eyes. In case of eye contact, flush eyes with water.

Stop use and ask doctor if irritation or redness developts, or if condition persists for more than 72 hours.

Directions

- Pump a small amount of foam into palm of hand
- Rub thoroughly over all surfaces of both hands
- Rub hands together briskly until dry

Inactive ingredients

Water, dihyroxypropyl PEG-5 linoleammonium chloride, glycereth-2 cocoate, behentrimonium chloride, dihydroxyethyl cocamine oxide, fragrance

Uses

For hand sanitizing to decrease bacteria on the skin
Recommended for repeated use

Keep out of reach of children. If swallowed, get medical help or contact a Poison Control Center right away.

PACKAGE LABEL

Afia Alcohol-Free Foaming Hand Sanitizer